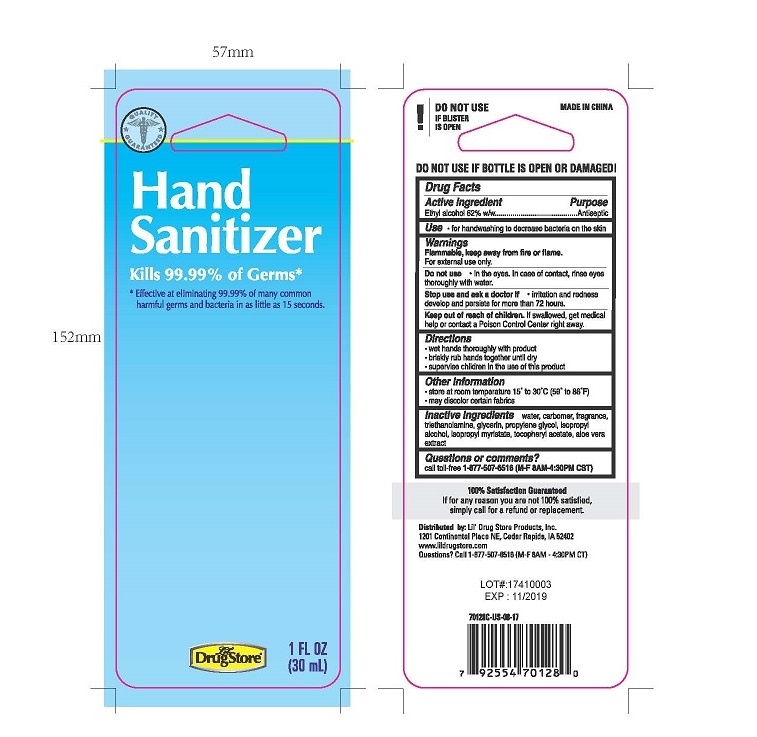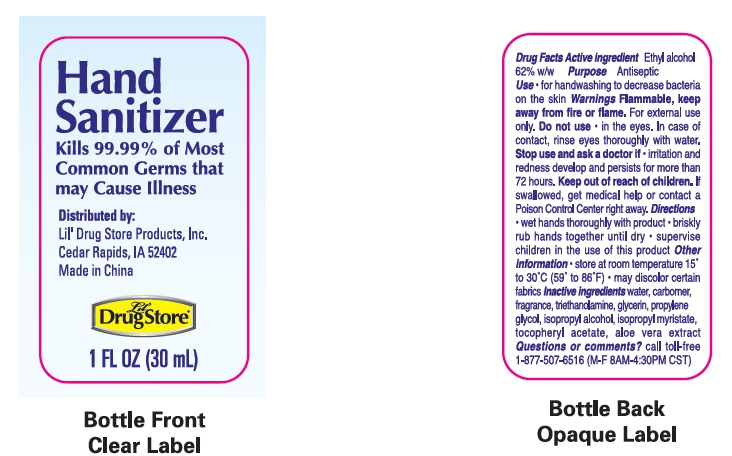 DRUG LABEL: Hand Sanitizer
NDC: 71927-001 | Form: GEL
Manufacturer: Orazen Inc
Category: otc | Type: HUMAN OTC DRUG LABEL
Date: 20171210

ACTIVE INGREDIENTS: ALCOHOL 62 mL/100 mL
INACTIVE INGREDIENTS: ISOPROPYL MYRISTATE; .ALPHA.-TOCOPHEROL ACETATE; ISOPROPYL ALCOHOL; WATER; ALOE VERA LEAF; GLYCERIN; PROPYLENE GLYCOL; CARBOMER INTERPOLYMER TYPE A (55000 CPS); TROLAMINE

Active Ingredient:
Ethyl Alcohol 62% w/w

Purpose

Antiseptic

Warnings

Flammable, keep away from fire or flame.

For external use only.

Stop use and ask a doctor if irritation and redness develops and persists for more that 72 hours.

Keep out of reach of children. If swallowed, get medical help or contact a Poison Control Center right away.

Directions

- Wet hands thoroughly with product
- Briskly rub hands together until dry
- Supervise children in the use of this product

Inactive Ingredients

water, carbomer, fragrance, triethanoamine, glycerin, propylene glycol, isopropyl alcohol, isopropyl myristate, tocopheryl acetate, aloe vera extract

Other Information

- Store at room temperature 15 to 30C (59 to 86F)
- May discolor certain fabrics

Use

For hand washing to decrease bacteria on the skin

Do not use in the eyes. In case of contact, rinse eyes thoroughly with water.